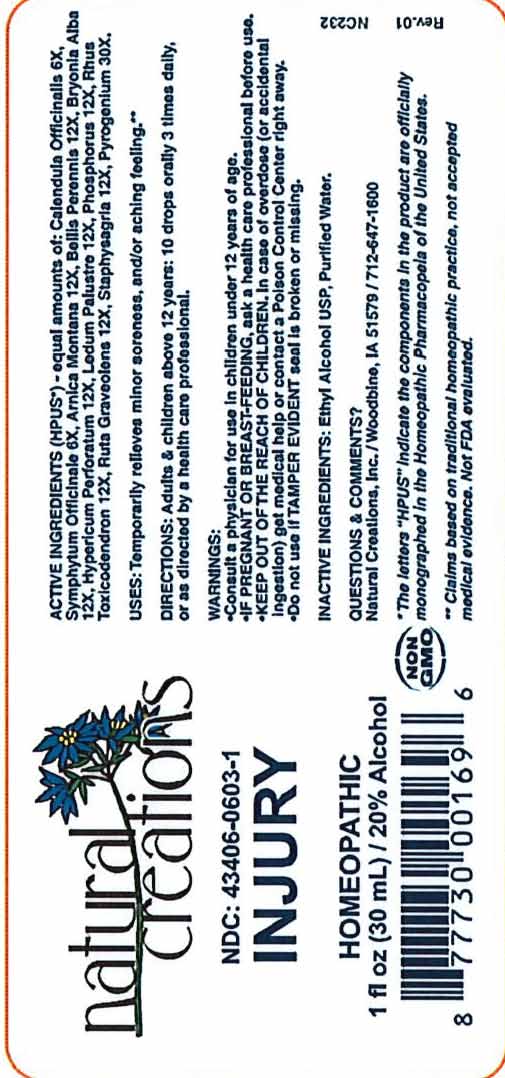 DRUG LABEL: Injury
NDC: 43406-0603 | Form: LIQUID
Manufacturer: Natural Creations, Inc
Category: homeopathic | Type: HUMAN OTC DRUG LABEL
Date: 20251216

ACTIVE INGREDIENTS: CALENDULA OFFICINALIS FLOWERING TOP 6 [hp_X]/1 mL; COMFREY ROOT 6 [hp_X]/1 mL; ARNICA MONTANA WHOLE 12 [hp_X]/1 mL; BELLIS PERENNIS WHOLE 12 [hp_X]/1 mL; BRYONIA ALBA ROOT 12 [hp_X]/1 mL; HYPERICUM PERFORATUM WHOLE 12 [hp_X]/1 mL; RHODODENDRON TOMENTOSUM LEAFY TWIG 12 [hp_X]/1 mL; PHOSPHORUS 12 [hp_X]/1 mL; TOXICODENDRON PUBESCENS LEAF 12 [hp_X]/1 mL; RUTA GRAVEOLENS FLOWERING TOP 12 [hp_X]/1 mL; DELPHINIUM STAPHISAGRIA SEED 12 [hp_X]/1 mL; RANCID BEEF 30 [hp_X]/1 mL
INACTIVE INGREDIENTS: ALCOHOL; WATER

Injury

ACTIVE INGREDIENT

ACTIVE INGREDIENTS (*HPUS) - equal amounts of: Calendula Officinalis 6X, Symphytum Officinale 6X, Arnica Montana 12X, Bellis Perennis 12X, Bryonia Alba 12X, Hypericum Perforatum 12X, Ledum Palustre 12X, Phosphorus 12X, Rhus Toxicodendron 12X, Ruta Graveolens 12X, Staphysagria 12X, Pyrogenium 30X

INDICATIONS AND USAGE

USES: Temporarily relieves minor soreness, and/or aching feeling.**

PURPOSE

USES: Temporarily relieves minor soreness, and/or aching feeling.**

DOSAGE AND ADMINISTRATION

DIRECTIONS: Adults & children above 12 years: 10 drops orally 3 times daily, or as directed by a health care professional.

KEEP OUT OF REACH OF CHILDREN

KEEP OUT OF THE REACH OF CHILDREN. In case of overdose (or accidental ingestion) get medical help or contact a Poison Control Center right away.

WARNINGS:

- Consult a physician for use in children under 12 years of age.
- IF PREGNANT OR BREAST-FEEDING, ask a health care professional before use.
- KEEP OUT OF THE REACH OF CHILDREN. In case of overdose (or accidental ingestion) get medical help or contact a Poison Control Center right away.
- Do not use if TAMPER EVIDENT seal is broken or missing.

INACTIVE INGREDIENTS: Ethyl Alcohol USP, Purified Water

QUESTIONS & COMMENTS?

Natural Creations, Inc. / Woodbine, IA 51579 / 712-647-1600

REFERENCES

*The letters "HPUS" indicate the components in the product are officially monographed in the Homeopathic Pharmacopeia of the United States.

**Claims based on traditional homeopathic practice, not accepted medical evidence. Not FDA evaluated.

PACKAGE LABEL

NDC:43406-0603-1

Injury

HOMEOPATHIC

1 fl oz (30mL) / 20% Alcohol